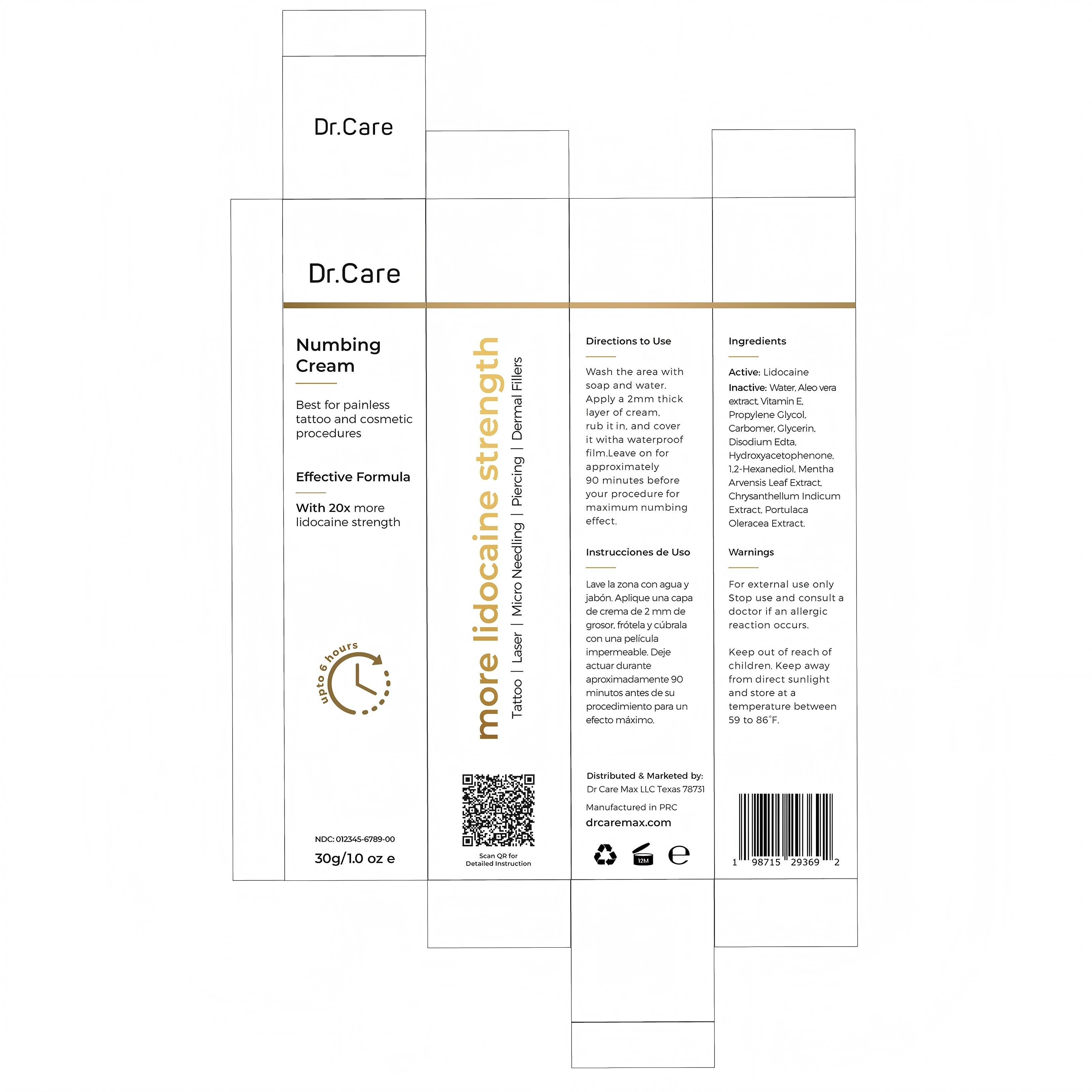 DRUG LABEL: 5% Dr.care Numb cream
NDC: 84019-028 | Form: CREAM
Manufacturer: Shengnan (Guangzhou) Cosmetics Co., LTD
Category: otc | Type: HUMAN OTC DRUG LABEL
Date: 20250304

ACTIVE INGREDIENTS: LIDOCAINE 100 mg/1 g
INACTIVE INGREDIENTS: GLYCERIN; CARBOMER; WATER

WARNINGS

For external use only.Stop use and consulta doctor if an allergicreaction occurs.
Keep out of reach of children. Keep away from direct sunlight and store at a temperature between 15 to 30'C(59 to 86'F).

PURPOSE

Best for painless tattoo and cosmetic procedures

STOP USE

Discontinueuse if signs of irritation or rash occur

ACTIVE INGREDIENT

5% Lidocaine

WHEN USING

Wash the area with soap and water.

INACTIVE INGREDIENT

Water, Aleo vera
extract, Vitamin E,Propylene Glycol,Carbomer, Glycerin,Disodium Edta.
Hydroxyacetophenone,
1.2-Hexanediol, Mentha Arvensis Leaf Extract,
Chrysanthellum
Indicum Extract,
Portulaca Oleracea Extract.

DOSAGE AND ADMINISTRATION

Apply 1-3 times a week

INDICATIONS AND USAGE

Apply a 2mm thick layer of cream, rub it in, and cover it with a waterproof film.Leave on for approximately 90 minutes before your procedure for maximum numbing effect.